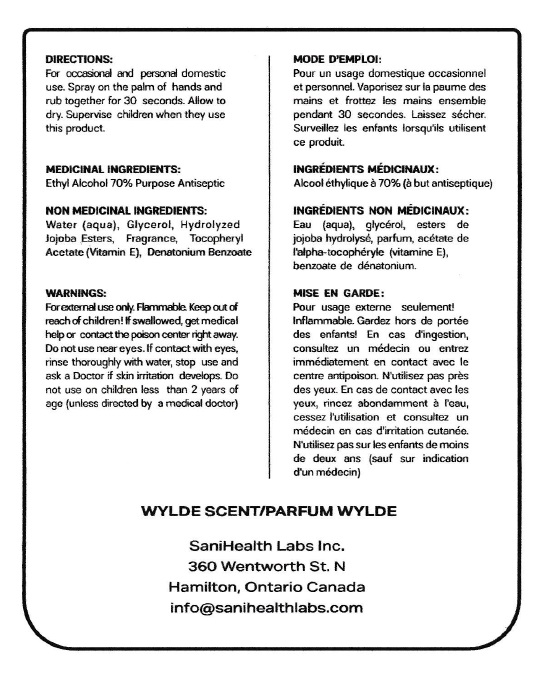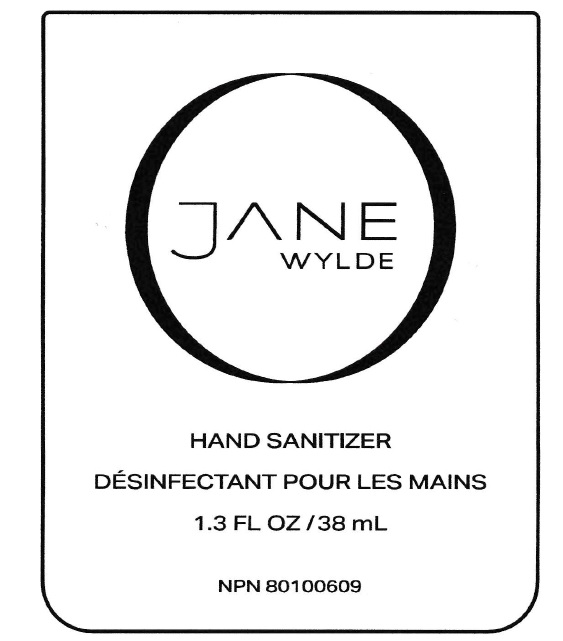 DRUG LABEL: Hand Sanitizer
NDC: 79861-005 | Form: GEL
Manufacturer: Sanihealth Labs Inc.
Category: otc | Type: HUMAN OTC DRUG LABEL
Date: 20210913

ACTIVE INGREDIENTS: ALCOHOL 80 mL/100 mL
INACTIVE INGREDIENTS: GLYCERIN; HYDROLYZED JOJOBA ESTERS (ACID FORM); WATER; .ALPHA.-TOCOPHEROL ACETATE; DENATONIUM BENZOATE

Jane Wylde Hand sanitizer

Active Ingredient(s)

Ethyl Alcohol 70% v/v. Purpose: Antiseptic

Purpose

Antiseptic, Hand Sanitizer

Use

Hand Sanitizer to help reduce bacteria that potentially can cause disease. For use when soap and water are not available.

Warnings

For external use only. Flammable. Keep away from heat or flame

Do not use

- in children less than 2 months of age
- on open skin wounds

When using this product keep out of eyes, ears, and mouth. In case of contact with eyes, rinse eyes thoroughly with water.
Stop use and ask a doctor if irritation or rash occurs. These may be signs of a serious condition.
Keep out of reach of children. If swallowed, get medical help or contact a Poison Control Center right away.

Stop use and ask a doctor if irritation or rash occurs. These may be signs of a serious condition.

Keep out of reach of children. If swallowed, get medical help or contact a Poison Control Center right away.

Directions

- For occasional and personal domestic use, spray on the palm of hands and rub together for 30 seconds. Allow to dry. Supervise children when they use this product.

Other information

- Store between 15-30C (59-86F)
- Avoid freezing and excessive heat above 40C (104F)

Inactive ingredients

Water, glycerol, hydrolyzed jojoba esters, fragrance, tocopheryl acetate, denatonium benzoate